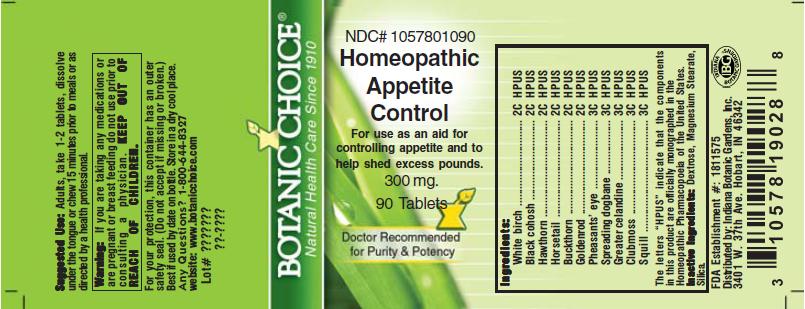 DRUG LABEL: Homeopathic Weight Loss Formula
NDC: 10578-010 | Form: TABLET
Manufacturer: Indiana Botanic Gardens
Category: homeopathic | Type: HUMAN OTC DRUG LABEL
Date: 20110325

ACTIVE INGREDIENTS: BETULA PUBESCENS LEAF 2 [hp_C]/1 1; BLACK COHOSH 2 [hp_C]/1 1; CRATAEGUS LAEVIGATA FRUIT 2 [hp_C]/1 1; EQUISETUM HYEMALE 2 [hp_C]/1 1; FRANGULA ALNUS BARK 2 [hp_C]/1 1; SOLIDAGO VIRGAUREA FLOWERING TOP 2 [hp_C]/1 1; ADONIS VERNALIS 3 [hp_C]/1 1; APOCYNUM ANDROSAEMIFOLIUM ROOT 3 [hp_C]/1 1; CHELIDONIUM MAJUS 3 [hp_C]/1 1; LYCOPODIUM CLAVATUM SPORE 3 [hp_C]/1 1; DRIMIA MARITIMA BULB 3 [hp_C]/1 1
INACTIVE INGREDIENTS: DEXTROSE; MAGNESIUM STEARATE ; SILICON DIOXIDE 

Homeopathic Appetite Control

ACTIVE INGREDIENT

I n g r e d i e n t s :

White birch................................. 2C HPUS
Black cohosh................... 2C HPUS
Hawthorn.................. 2C HPUS
Horsetail.................... 2C HPUS
Buckthorn...................... 2C HPUS
Goldenrod...................... 2C HPUS
Pheasants' eye.......................... 3C HPUS

Spreading dogbane.......3C HPUS

Greater celandine......................3C HPUS

Clubmoss.................3C HPUS

Squill............................3C HPUS

The letters “HPUS” indicate that the components in
this product are officially monographed in the
Homeopathic Pharmacopoeia of the United States.

PURPOSE

For use as an aid in controlling appetite and to help shed excess pounds

KEEP OUT OF
REACH OF CHILDREN.

INDICATIONS AND USAGE

For use as an aid in controlling appetite and to help shed excess pounds

WARNINGS

Warning: If you are taking any medications or
are pregnant or breast feeding do not use prior to
consulting a physician.

DOSAGE AND ADMINISTRATION

Suggested Use: Adults, take 1-2 tablets, dissolve under tongue or
chew 15 minutes prior to meals or as directed by a health care professional.

Inactive Ingredients: Dextrose, Magnesium
Stearate, Silica.

PACKAGE LABEL

NDC# 1057801090

Homeopathic Appetite Control

For use as an aid in controlling appetite and to help shed excess pounds

300 mg.
90 Tablets

USER SAFETY WARNINGS

For your protection, this container has an outer
safety seal. (Do not accept if missing or broken.)
Best if used by date on bottle. Store in a dry cool place.
Any Questions? 1-800-644-8327
website: www.botanicchoice.com

FDA Establishment #: 1811575

Distributed by: Indiana Botanic Gardens, Inc.
3401 W. 37th Ave. Hobart, IN 46342